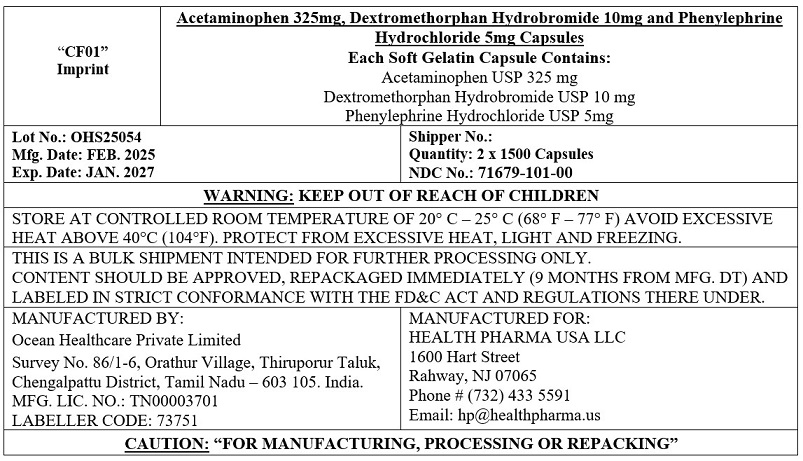 DRUG LABEL: Acetaminophen 325 mg, Dextromethorphan Hydrobromide 10 mg, Phenlyephrine Hydrochloride 5 mg softgel (DAY-TIME)
NDC: 71679-101 | Form: CAPSULE, LIQUID FILLED
Manufacturer: Health Pharma USA LLC
Category: otc | Type: HUMAN OTC DRUG LABEL
Date: 20250924

ACTIVE INGREDIENTS: ACETAMINOPHEN 325 mg/1 1; DEXTROMETHORPHAN HYDROBROMIDE 10 mg/1 1; PHENYLEPHRINE HYDROCHLORIDE 5 mg/1 1
INACTIVE INGREDIENTS: FD&C RED NO. 40; FD&C YELLOW NO. 6; GELATIN; GLYCERIN; POLYETHYLENE GLYCOL 400; POVIDONE K30; PROPYLENE GLYCOL; WATER; SORBITOL SOLUTION; SORBITAN

Acetaminophen 325 mg, Dextromethorphan Hydrobromide 10 mg, Phenlyephrine Hydrochloride 5 mg softgel (DAY-TIME)

Active ingredients (in each softgels)

Acetaminophen, USP 325 mg

Dextromethorphan Hydrobromide, USP 10 mg

Phenlyephrine Hydrochloride, USP 5 mg

Purpose

Pain reliever/fever reducer

Cough suppressant

Nasal decongestant

Uses

Temporarily relieves common cold and flu symptoms:

- nasal congestion
- cough due to minor throat and bronchial irritation
- headache
- minor aches and pains
- fever
- sore throat

Warnings

Liver warning:This product contains acetaminophen. Severe liver damage may occur if you take:

- more than 4 doses in 24 hours, which is the maximum daily amount for this product
- with other drugs containing acetaminophen
- 3 or more alcoholic drinks every day while using this product

Allergy alert:Acetaminophen may cause severe skin reactions. Symptoms may include:

- skin reddening
- blisters
- rash

If a skin reaction occurs, stop use and seek medical help right away.

Sore throat warning:If sore throat is severe, persists for more than 2 days, is accompanied or followed by fever, headache, rash, nausea, or vomiting, consult a doctor promptly.

Do not use

- with any other drug containing acetaminophen (prescription or non-prescription).
- if you are not sure whether a drug contains acetaminophen, ask a doctor or pharmacist.
- if you are now taking a prescription monoamine oxidase inhibitor (MAOI) (certain drugs for depression, psychiatric or emotional conditions, or Parkinson’s disease), or for 2 weeks after stopping the MAOI drug. If you do not know if your prescription drug contains an MAOI, ask a doctor or pharmacist before taking this product.
- if you have ever had an allergic reaction to this product or any of its ingredients

Ask a doctor before use if you have

- liver disease
- heart disease
- high blood pressure
- thyroid disease
- diabetes
- trouble urinating due to an enlarged prostate gland
- cough that occurs with too much phlegm (mucus)
- persistent or chronic cough such as occurs with smoking, asthma or emphysema

Ask a doctor or pharmacist before use if you aretaking the blood thinning drug warfarin

When using this product, do not use more than directed.

Stop use and ask a doctor if

- you get nervous, dizzy or sleepless
- pain, nasal congestion or cough gets worse or lasts more than 7 days
- fever gets worse or lasts more than 3 days
- redness or swelling is present
- new symptoms occur
- cough comes back or occurs with rash or headache that lasts. These could be signs of a serious condition.

If pregnant or breast-feeding,ask a health professional before use.

Keep out of reach of children

In case of overdose, get medical help or contact a Poison Control Center (1-800-222-122) right away. Quick medical attention is critical for adults and for children even if you do not notice any signs or symptoms.

Direction

- take only as directed
- do not exceed 4 doses per 24 hours

adults and children 12 years and over | take 2 softgels with water every 4 hours
children 4 to under 12 years | ask a doctor
children under 4 years | do not use

Other information

- store at room temperature.
- DO NOT USE IF PRINTED SEAL UNDER CAP IS MISSING OR DAMAGED

Inactive ingredients

FD&C red #40, FD&C yellow #6, Gelatin, Glycerin, Polyethylene Glycol 400, Povidone K30, Propylene Glycol, Purified Water, Sorbitol Sorbitan Solution.

Questions?

call toll-free 1-844-832-1138